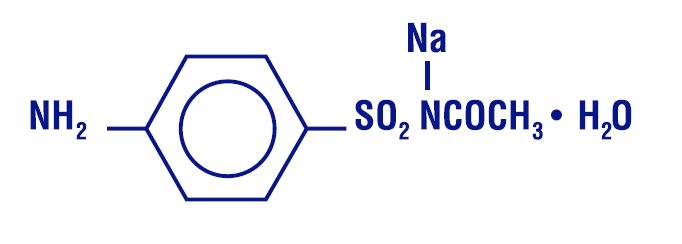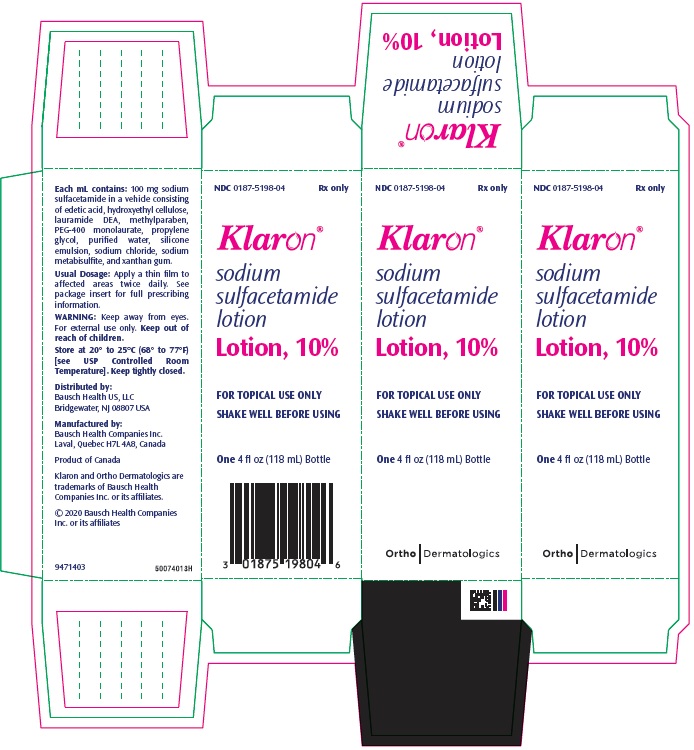 DRUG LABEL: Klaron
NDC: 0187-5198 | Form: LOTION
Manufacturer: Bausch Health US, LLC
Category: prescription | Type: HUMAN PRESCRIPTION DRUG LABEL
Date: 20200831

ACTIVE INGREDIENTS: sulfacetamide sodium 100 mg/1 mL
INACTIVE INGREDIENTS: EDETIC ACID; HYDROXYETHYL CELLULOSE (2000 MPA.S AT 1%); LAURIC DIETHANOLAMIDE; methylparaben; water; sodium chloride; sodium metabisulfite; xanthan gum; PEG-8 LAURATE; PROPYLENE GLYCOL

Klaron®
sodium sulfacetamide lotion
Lotion, 10%

DESCRIPTION

Each mL of Klaron® (sodium sulfacetamide lotion) Lotion, 10% contains 100 mg of sodium sulfacetamide in a vehicle consisting of edetic acid, hydroxyethyl cellulose, lauramide DEA, methylparaben, PEG-400 monolaurate, propylene glycol, purified water, silicone emulsion, sodium chloride, sodium metabisulfite, and xanthan gum.

Sodium sulfacetamide is a sulfonamide with antibacterial activity. Chemically, sodium sulfacetamide is N’ -[(4-amino phenyl) sulfonyl] - acetamide, monosodium salt, monohydrate. The structural formula is:

CLINICAL PHARMACOLOGY

The most widely accepted mechanism of action of sulfonamides is the Woods-Fildes theory, based on sulfonamides acting as a competitive inhibitor of para-aminobenzoic acid (PABA) utilization, an essential component for bacterial growth. While absorption through intact skin in humans has not been determined, in vitro studies with human cadaver skin indicated a percutaneous absorption of about 4%. Sodium sulfacetamide is readily absorbed from the gastrointestinal tract when taken orally and excreted in the urine largely unchanged. The biological half-life has been reported to be between 7 to 13 hours.

PHARMACOKINETICS

The pharmacokinetics of sulfacetamide and its major metabolite sulfaniliamide in Klaron Lotion was evaluated in adult subjects (N=14) with acne vulgaris. The subjects applied Klaron Lotion to their face, back, chest, and shoulders every 12 hours for 28 days. The percentage of the applied dose of Klaron Lotion excreted in the urine as sulfacetamide plus sulfanilamide ranged from 0.08 to 0.33%.

INDICATIONS

Klaron Lotion is indicated in the topical treatment of acne vulgaris.

CONTRAINDICATIONS

Klaron Lotion is contraindicated for use by patients having known hypersensitivity to sulfonamides or any other component of this preparation (see WARNINGS).

WARNINGS

Fatalities have occurred, although rarely, due to severe reactions to sulfonamides including Stevens-Johnson syndrome, toxic epidermal necrolysis, fulminant hepatic necrosis, agranulocytosis, aplastic anemia, and other blood dyscrasias. Hypersensitivity reactions may occur when a sulfonamide is readministered, irrespective of the route of administration. Sensitivity reactions have been reported in individuals with no prior history of sulfonamide hypersensitivity. At the first sign of hypersensitivity, skin rash, or other reactions, discontinue use of this preparation (see ADVERSE REACTIONS).

Klaron Lotion contains sodium metabisulfite, a sulfite that may cause allergic-type reactions including anaphylactic symptoms and life-threatening or less severe asthmatic episodes in certain susceptible people. The overall prevalence of sulfite sensitivity in the general population is unknown and probably low. Sulfite sensitivity is seen more frequently in asthmatic than in non-asthmatic people (see CONTRAINDICATIONS).

PRECAUTIONS

General

For external use only. Keep away from eyes. If irritation develops, use of the product should be discontinued and appropriate therapy instituted. Patients should be carefully observed for possible local irritation or sensitization during long-term therapy. Hypersensitivity reactions may occur when a sulfonamide is readministered irrespective of the route of administration, and cross-sensitivity between different sulfonamides may occur. Sodium sulfacetamide can cause reddening and scaling of the skin. Particular caution should be employed if areas of involved skin to be treated are denuded or abraded.

Keep out of reach of children.

Carcinogenesis, Mutagenesis, Impairment of Fertility

Long-term studies in animals have not been performed to evaluate carcinogenic potential.

Animal reproduction studies have not been conducted with Klaron Lotion. It is also not known whether Klaron Lotion can cause fetal harm when administered to a pregnant woman or can affect reproduction capacity. Klaron Lotion should be given to a pregnant woman only if clearly needed.

Kernicterus may occur in the newborn as a result of treatment of a pregnant woman at term with orally administered sulfonamide. There are no adequate and well-controlled studies of Klaron Lotion in pregnant women, and it is not known whether topically applied sulfonamides can cause fetal harm when administered to a pregnant woman.

Nursing Mothers

It is not known whether sodium sulfacetamide is excreted in human milk following topical use of Klaron Lotion. Systemically administered sulfonamides are capable of producing kernicterus in the infants of lactating women. Small amounts of orally administered sulfonamides have been reported to be eliminated in human milk. Because many drugs are excreted in human milk, caution should be exercised in prescribing for nursing women.

Pediatric Use

Safety and effectiveness in pediatric patients under the age of 12 have not been established.

ADVERSE REACTIONS

In controlled clinical trials for the management of acne vulgaris, the occurrence of adverse reactions associated with the use of Klaron Lotion was infrequent and restricted to local events. The total incidence of adverse reactions reported in these studies was less than 2%. Only one of 105 patients treated with Klaron Lotion had adverse reactions of erythema, itching, and edema. It has been reported that sodium sulfacetamide may cause local irritation, stinging, and burning. While the irritation may be transient, occasionally the use of medication has to be discontinued.

To report SUSPECTED ADVERSE REACTIONS, contact Bausch Health US, LLC at 1-800-321-4576 or FDA at 1-800-FDA-1088 or www.fda.gov/medwatch.

DOSAGE AND ADMINISTRATION

Apply a thin film to affected areas twice daily.

HOW SUPPLIED

4 fl oz (118 mL) Bottles NDC 0187-5198-04

Store at 20° to 25°C (68° to 77°F) [see USP Controlled Room Temperature]. Shake well before using. Keep tightly closed.

Distributed by:
Bausch Health US, LLC
Bridgewater, NJ 08807 USA

Manufactured by:
Bausch Health Companies Inc.
Laval, Quebec H7L 4A8, Canada

Klaron is a trademark of Bausch Health Companies Inc. or its affiliates.

© 2020 Bausch Health Companies Inc. or its affiliates
9471505
Rev. 08/2020

PRINCIPAL DISPLAY PANEL - 118 mL Bottle Carton

NDC 0187-5198-04
Rx only

Klaron®
sodium
sulfacetamide
lotion

Lotion, 10%

FOR TOPICAL USE ONLY
SHAKE WELL BEFORE USING

One 4 fl oz (118 mL) Bottle
Ortho Dermatologics